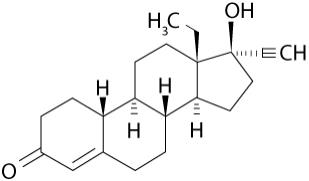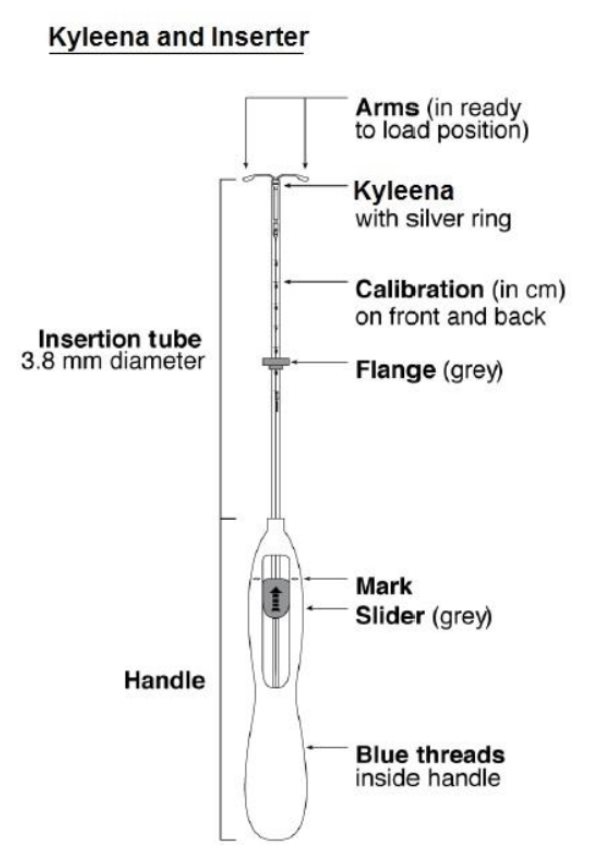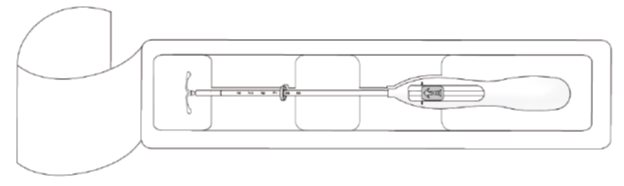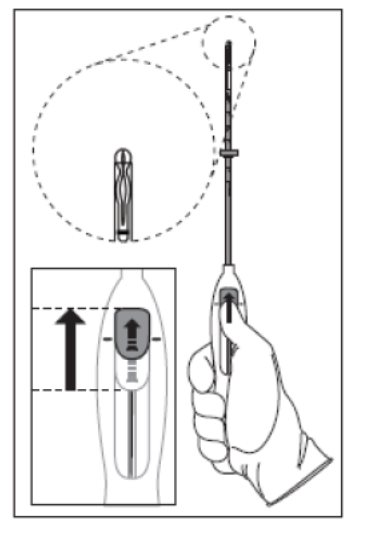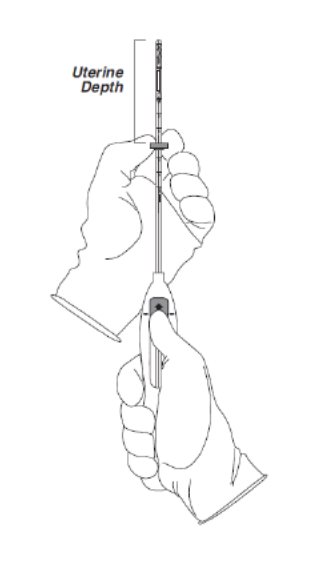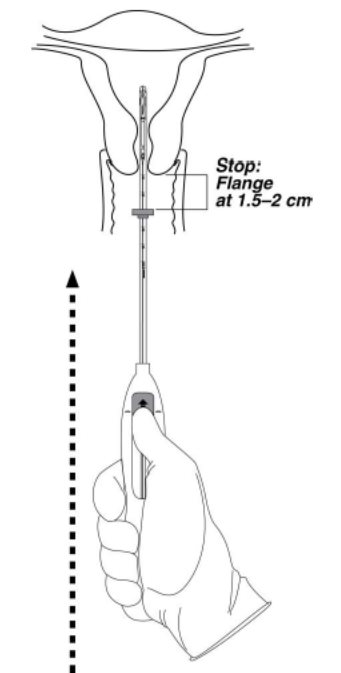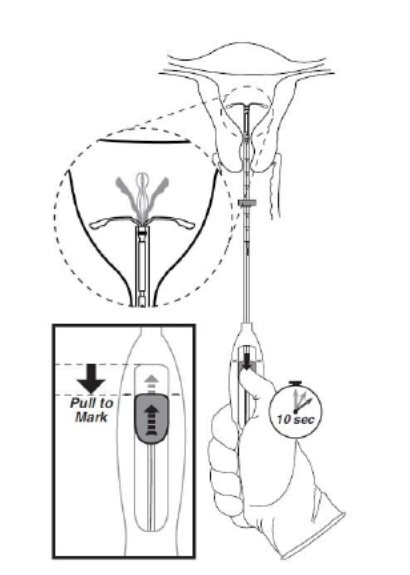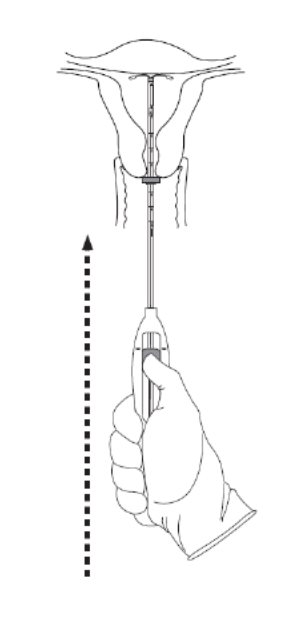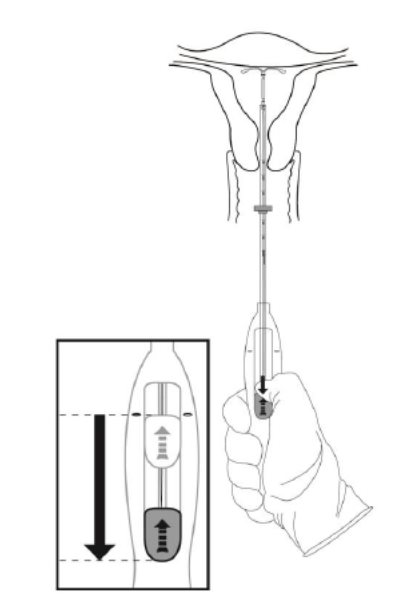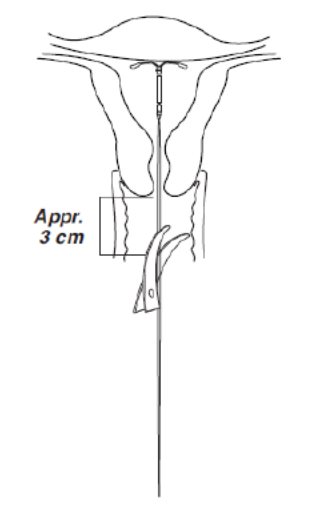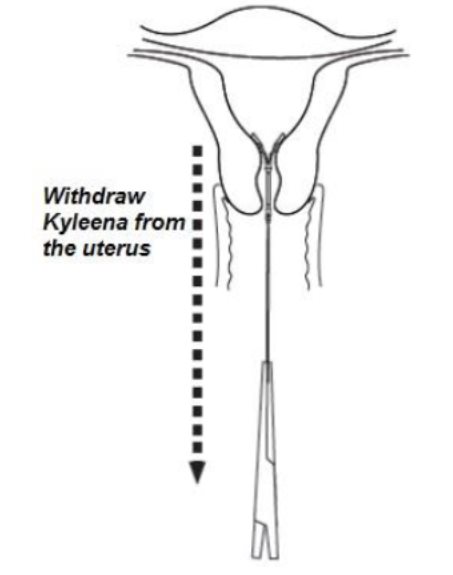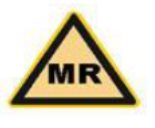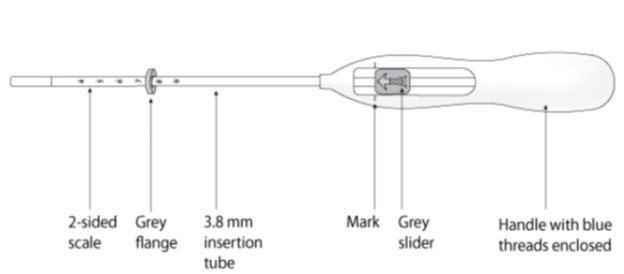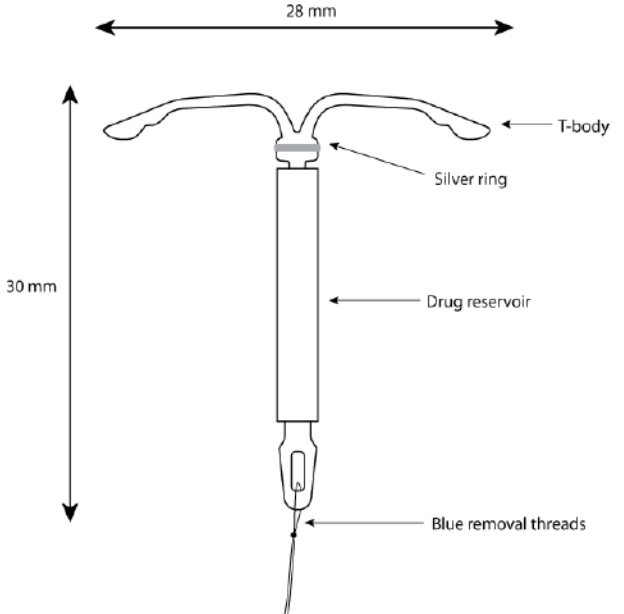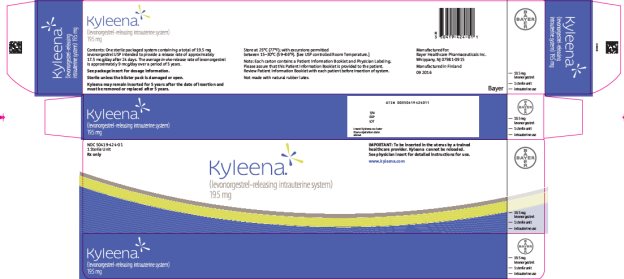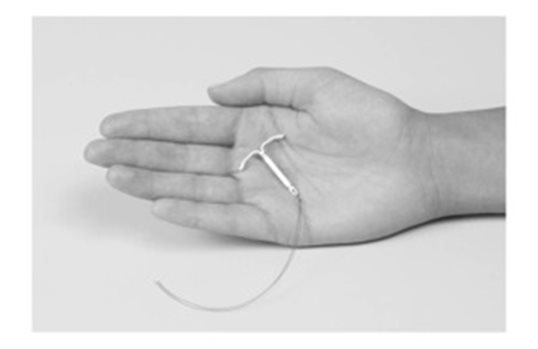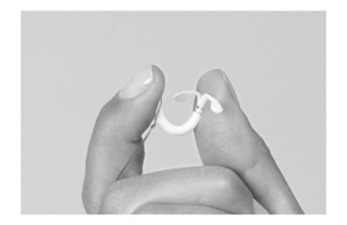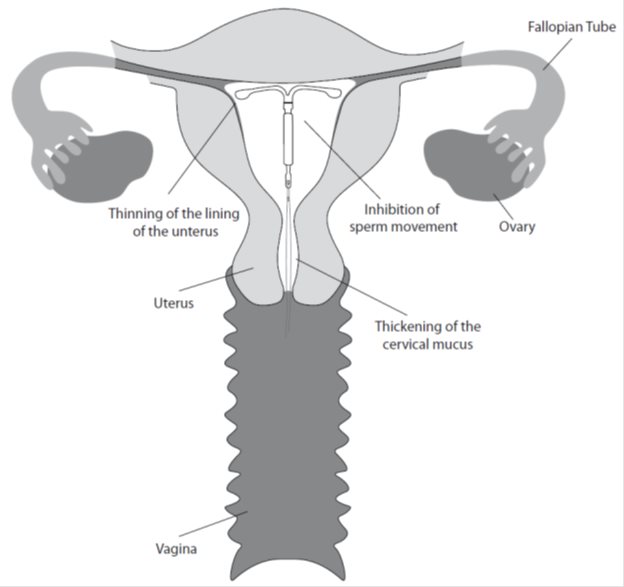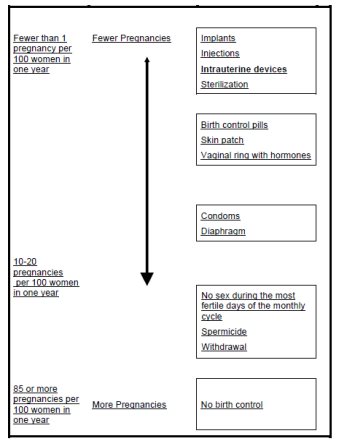 DRUG LABEL: Kyleena
NDC: 50419-424 | Form: INTRAUTERINE DEVICE
Manufacturer: Bayer HealthCare Pharmaceuticals Inc.
Category: prescription | Type: HUMAN PRESCRIPTION DRUG LABEL
Date: 20251023

ACTIVE INGREDIENTS: LEVONORGESTREL 19.5 mg/1 1
INACTIVE INGREDIENTS: DIMETHICONE; BARIUM SULFATE

HIGHLIGHTS OF PRESCRIBING INFORMATION

These highlights do not include all the information needed to use KYLEENA safely and effectively. See full prescribing information for KYLEENA.
KYLEENA (levonorgestrel-releasing intrauterine system)
Initial U.S. Approval: 2000

RECENT MAJOR CHANGES

Dosage and Administration (2.4) 3/2023

1 INDICATIONS AND USAGE

Kyleena is a progestin-containing intrauterine system (IUS) indicated for prevention of pregnancy for up to 5 years. (1)

2 DOSAGE AND ADMINISTRATION

- Release rate of levonorgestrel (LNG) is 17.5 mcg/day after 24 days and declines to 7.4 mcg/day after 5 years; Kyleena must be removed or replaced after 5 years. (2.1)
- To be inserted by a trained healthcare provider using strict aseptic technique. Follow insertion instructions exactly as described. (2.2)
- Patient should be re-examined and evaluated 4 to 6 weeks after insertion; then yearly or more often if clinically indicated. (2.3)

3 DOSAGE FORMS AND STRENGTHS

- One sterile intrauterine system consisting of a T-shaped polyethylene frame with a steroid reservoir containing 19.5 mg levonorgestrel, packaged within a sterile inserter (3)

4 CONTRAINDICATIONS

- Pregnancy or suspicion of pregnancy. Cannot be used for post-coital contraception (emergency contraception) (4)
- Congenital or acquired uterine anomaly if it distorts the uterine cavity (4)
- Acute pelvic inflammatory disease (PID) or a history of PID unless there has been a subsequent intrauterine pregnancy (4)
- Postpartum endometritis or infected abortion in the past 3 months (4)
- Known or suspected uterine or cervical malignancy (4)
- Known or suspected breast cancer or other progestin-sensitive cancer (4)
- Uterine bleeding of unknown etiology (4)
- Untreated acute cervicitis or vaginitis or other lower genital tract infections (4)
- Acute liver disease or liver tumor (benign or malignant) (4)
- Increased susceptibility to pelvic infection (4)
- A previous intrauterine device (IUD) that has not been removed (4)
- Hypersensitivity to any component of Kyleena (4)

5 WARNINGS AND PRECAUTIONS

- Remove Kyleena if pregnancy occurs with Kyleena in place. If pregnancy occurs, there is increased risk of ectopic pregnancy including loss of fertility, pregnancy loss, septic abortion (including septicemia, shock and death), and premature labor and delivery. (5.1, 5.2)
- Group A streptococcal infection has been reported following insertion of LNG IUS; strict aseptic technique is essential during insertion. (5.3)
- Before using Kyleena, consider the risks of PID. (5.4)
- Uterine perforation may occur and may reduce contraceptive effectiveness or require surgery. Risk is increased if inserted in lactating women and may be increased if inserted in women with fixed retroverted uteri and postpartum. (5.5)
- Partial or complete expulsion may occur, which can be unnoticed, leading to loss of contraceptive efficacy. (5.6)
- Evaluate persistent enlarged ovarian follicles or ovarian cysts. (5.7)
- Bleeding patterns become altered, may remain irregular and amenorrhea may ensue. (5.8)
- Kyleena can be safely scanned with MRI only under certain conditions. (5.11)

6 ADVERSE REACTIONS

The most common adverse reactions reported (≥ 5% users) were vulvovaginitis, ovarian cysts, abdominal pain/pelvic pain, headache/migraine, acne/seborrhea, dysmenorrhea/uterine spasm, breast pain/breast discomfort, and increased bleeding. (6)

To report SUSPECTED ADVERSE REACTIONS, contact Bayer HealthCare Pharmaceuticals Inc. at 1-888-842-2937 or FDA at 1-800-FDA-1088 or www.fda.gov/medwatch.

FULL PRESCRIBING INFORMATION

1 INDICATIONS AND USAGE

Kyleena is indicated to prevent pregnancy for up to 5 years. Replace the system after 5 years if continued use is desired.

2 DOSAGE AND ADMINISTRATION

2.1 Dosing Over Time

Kyleena contains 19.5 mg of levonorgestrel (LNG) released in vivo at a rate of approximately 17.5 mcg/day after 24 days. This rate decreases progressively to 9.8 mcg/day after 1 year and to 7.4 mcg/day after 5 years. The average in vivo release rate of LNG is approximately 12.6 mcg/day over the first year and 9.0 mcg/day over a period of 5 years. [See Clinical Pharmacology (12.3).]

Kyleena must be removed by the end of the fifth year and can be replaced at the time of removal with a new Kyleena if continued contraceptive protection is desired.

Kyleena can be physically distinguished from other intrauterine systems (IUSs) by the combination of the visibility of the silver ring on ultrasound and the blue color of the removal threads.

Kyleena is supplied in a sterile package within an inserter that enables single-handed loading (see Figure 1). Do not open the package until required for insertion [see Description (11.2)]. Do not use if the seal of the sterile package is broken or appears compromised. Use strict aseptic techniques throughout the insertion procedure [see Warnings and Precautions (5.3)].

2.2. Insertion Instructions

- Obtain a complete medical and social history to determine conditions that might influence the selection of a levonorgestrel-releasing intrauterine system (LNG IUS) for contraception. If indicated, perform a physical examination and appropriate tests for any forms of genital or other sexually transmitted infections. [See Contraindications (4) and Warnings and Precautions (5.10).] Because irregular bleeding/spotting is common during the first months of Kyleena use, exclude endometrial pathology (polyps or cancer) prior to the insertion of Kyleena in women with persistent or uncharacteristic bleeding [see Warnings and Precautions (5.8)].
- Follow the insertion instructions exactly as described to ensure proper placement and avoid premature release of Kyleena from the inserter. Once released, Kyleena cannot be re-loaded.
- Check expiration date of Kyleena prior to initiating insertion.
- Kyleena should be inserted by a trained healthcare provider. Healthcare providers should become thoroughly familiar with the insertion instructions before attempting insertion of Kyleena.
- Insertion may be associated with some pain and/or bleeding or vasovagal reactions (for example, syncope, bradycardia), or with seizure, especially in patients with a predisposition to these conditions. Consider administering analgesics prior to insertion.

Timing of Insertion

Table 1: When to Insert Kyleena
Starting Kyleena in women not currently using hormonal or intrauterine contraception | - Insert Kyleena any time there is reasonable certainty that the woman is not pregnant. Consider the possibility of ovulation and conception prior to initiation of this product [see Contraindications (4)]. - If Kyleena is inserted during the first seven days of the menstrual cycle or immediately after a first trimester abortion, back-up contraception is not needed. - If Kyleena is not inserted during the first seven days of the menstrual cycle, a barrier method of contraception should be used, or the patient should abstain from vaginal intercourse for seven days to prevent pregnancy.
Switching to Kyleena from an oral, transdermal or vaginal hormonal contraceptive | - Insert Kyleena at any time, including during the hormone-free interval of the previous method. - If inserted during active use of the previous method, continue that method for 7 days after Kyleena insertion or until the end of the current treatment cycle. - If the woman was using continuous hormonal contraception, discontinue that method seven days after Kyleena insertion.
Switching to Kyleena from an injectable progestin contraceptive | - Insert Kyleena at any time; a non-hormonal back-up birth control (such as condoms or spermicide) should also be used for 7 days if Kyleena is inserted more than 3 months (13 weeks) after the last injection.
Switching to Kyleena from a contraceptive implant or another IUS | - Insert Kyleena on the same day the implant or IUS is removed. - Insert Kyleena at any time during the menstrual cycle.
Inserting Kyleena after first trimester abortion or miscarriage | - Insert Kyleena immediately after a first-trimester abortion or miscarriage, unless it is a septic abortion [see Contraindications (4)].
Inserting Kyleena after childbirth or second-trimester abortion or miscarriage
- Immediate insertion after childbirth or second-trimester abortion or miscarriage | - Insert Kyleena after removal of the placenta. Back-up contraception is not needed. [See Contraindications (4), Warnings and Precautions (5.5, 5.6), Adverse Reactions (6.2)].
Interval insertion following complete involution of the uterus | - Wait a minimum of 6 weeks or until the uterus is fully involuted before inserting Kyleena [see Warnings and Precautions (5.5, 5.6), Adverse Reactions (6.2)]. - Insert Kyleena any time there is reasonable certainty the woman is not pregnant. - If Kyleena is not inserted during the first 7 days of the menstrual cycle, a back-up method of contraception should be used, or the woman should abstain from vaginal intercourse for 7 days to prevent pregnancy [see Contraindications (4), Warnings and Precautions (5.2)].

Tools for Insertion

Note: The inserter provided with Kyleena (see Figure 1) and the Insertion Procedure described in this section are not applicable for immediate insertion after childbirth or second-trimester abortion or miscarriage. For immediate insertion, remove Kyleena from the inserter by first loading (see Figure 2) and then releasing (see Figure 7) Kyleena from the inserter, and insert according to accepted practice.

Preparation

- Gloves
- Speculum
- Sterile uterine sound
- Sterile tenaculum
- Antiseptic solution, applicator

Procedure

- Sterile gloves
- Kyleena with inserter in sealed package
- Instruments and anesthesia for paracervical block, if anticipated
- Consider having an unopened back-up Kyleena available
- Sterile, sharp curved scissors

Preparation for insertion

- Exclude pregnancy and confirm that there are no other contraindications to the use of Kyleena.
- With the patient comfortably in lithotomy position, do a bimanual exam to establish the size, shape and position of the uterus.
- Gently insert a speculum to visualize the cervix.
- Thoroughly cleanse the cervix and vagina with a suitable antiseptic solution.
- Prepare to sound the uterine cavity. Grasp the upper lip of the cervix with a tenaculum forceps and gently apply traction to stabilize and align the cervical canal with the uterine cavity. Perform a paracervical block if needed. If the uterus is retroverted, it may be more appropriate to grasp the lower lip of the cervix. The tenaculum should remain in position and gentle traction on the cervix should be maintained throughout the insertion procedure.
- Gently insert a uterine sound to check the patency of the cervix, measure the depth of the uterine cavity in centimeters, confirm cavity direction, and detect the presence of any uterine anomaly. If you encounter difficulty or cervical stenosis, use dilatation, and not force, to overcome resistance. If cervical dilatation is required, consider using a paracervical block.

Insertion Procedure

Proceed with insertion only after completing the above steps and ascertaining that the patient is appropriate for Kyleena. Ensure use of aseptic technique throughout the entire procedure.

Step 1–Opening of the package

- Open the package (Figure 1). The contents of the package are sterile.

Figure 1. Opening the Kyleena Package

- Using sterile gloves, lift the handle of the sterile inserter and remove from the sterile package.

Step 2–Load Kyleena into the insertion tube

- Push the slider forward as far as possible in the direction of the arrow, thereby moving the insertion tube over the Kyleena T-body to load Kyleena into the insertion tube (Figure 2). The tips of the arms will meet to form a rounded end that extends slightly beyond the insertion tube.

Figure 2. Move slider all the way to the forward position to load Kyleena

- Maintain forward pressure with your thumb or forefinger on the slider. DO NOT move the slider downward at this time as this may prematurely release the threads of Kyleena. Once the slider is moved below the mark, Kyleena cannot be re-loaded.

Step 3–Setting the Flange

- Holding the slider in this forward position, set the upper edge of the flange to correspond to the uterine depth (in centimeters) measured during sounding (Figure 3).

Figure 3. Setting the flange

Step 4–Kyleena is now ready to be inserted

- Continue holding the slider in this forward position. Advance the inserter through the cervix until the flange is approximately 1.5–2 cm from the cervix and then pause (Figure 4).

Figure 4. Advancing insertion tube until flange is 1.5 to 2 cm from the cervix

Do not force the inserter. If necessary, dilate the cervical canal.

Step 5–Open the arms

- While holding the inserter steady, move the slider down to the mark to release the arms of Kyleena (Figure 5). Wait 10 seconds for the horizontal arms to open completely.

Figure 5. Move the slider back to the mark to release and open the arms

Step 6–Advance to fundal position

Advance the inserter gently towards the fundus of the uterus until the flange touches the cervix. If you encounter fundal resistance do not continue to advance. Kyleena is now in the fundal position (Figure 6). Fundal positioning of Kyleena is important to prevent expulsion.

Figure 6. Move Kyleena into the fundal position

Step 7–Release Kyleena and withdraw the inserter

- Holding the entire inserter firmly in place, release Kyleena by moving the slider all the way down (Figure 7).

Figure 7. Move the slider all the way down to release Kyleena from the insertion tube

- Continue to hold the slider all the way down while you slowly and gently withdraw the inserter from the uterus.
- Using a sharp, curved scissor, cut the threads perpendicular, leaving about 3 cm visible outside of the cervix [cutting threads at an angle may leave sharp ends (Figure 8)]. Do not apply tension or pull on the threads when cutting to prevent displacing Kyleena.

Figure 8. Cutting the threads

Kyleena insertion is now complete. Prescribe analgesics, if indicated. Record the Kyleena lot number in the patient records.

Important information to consider during or after insertion

- If you suspect that Kyleena is not in the correct position, check placement (for example, using transvaginal ultrasound). Remove Kyleena if it is not positioned completely within the uterus. Do not reinsert a removed Kyleena.
- If there is clinical concern, exceptional pain or bleeding during or after insertion, take appropriate steps (such as physical examination and ultrasound) immediately to exclude perforation.

2.3 Patient Follow-up

- Reexamine and evaluate patients 4 to 6 weeks after insertion and once a year thereafter, or more frequently if clinically indicated.

2.4 Removal of Kyleena

Timing of Removal

- Kyleena should not remain in the uterus after 5 years.
- If pregnancy is not desired, remove Kyleena during the first 7 days of the menstrual cycle, provided the woman is still experiencing regular menses. If removal will occur at other times during the cycle or the woman does not experience regular menses, she is at risk of pregnancy; start a new contraceptive method a week prior to removal for these women. [See Dosage and Administration (2.5).]

Tools for Removal

Preparation

- Gloves
- Speculum

Procedure

- Sterile forceps

Removal Procedure

- Remove Kyleena by applying gentle traction on the threads with forceps (Figure 9).

Figure 9. Removal of Kyleena

- If the threads are not visible, determine location of Kyleena by ultrasound [see Warnings and Precautions (5.10)].
- If Kyleena is found to be in the uterine cavity on ultrasound exam, it may be removed using a narrow forceps, such as an alligator forceps. This may require dilation of the cervical canal. After removal of Kyleena, examine the system to ensure that it is intact.
- If unable to remove with gentle traction, determine Kyleena location and exclude perforation by ultrasound or other imaging [see Warnings and Precautions (5.10)].
- Removal may be associated with some:
  - pain and/or bleeding or vasovagal reactions (for example, syncope, bradycardia) or seizure, especially in patients with a predisposition to these conditions.
  - breakage or embedment of Kyleena in the myometrium that can make removal difficult [see Warnings and Precautions (5.5)]. Analgesia, paracervical anesthesia, cervical dilation, alligator forceps or other grasping instrument, or hysteroscopy may be used to assist in removal.

2.5 Continuation of Contraception after Removal

- If pregnancy is not desired and if a woman wishes to continue using Kyleena, a new system can be inserted immediately after removal any time during the cycle.
- If a patient with regular cycles wants to start a different contraceptive method, time removal and initiation of the new method to ensure continuous contraception. Either remove Kyleena during the first 7 days of the menstrual cycle and start the new method immediately thereafter or start the new method at least 7 days prior to removing Kyleena if removal is to occur at other times during the cycle.
- If a patient with irregular cycles or amenorrhea wants to start a different contraceptive method, start the new method at least 7 days before removal.

3 DOSAGE FORMS AND STRENGTHS

Kyleena is a LNG-releasing IUS (a type of intrauterine device, or IUD) consisting of a T-shaped polyethylene frame with a steroid reservoir containing a total of 19.5 mg LNG.

4 CONTRAINDICATIONS

The use of Kyleena is contraindicated when one or more of the following conditions exist:

- Pregnancy or suspicion of pregnancy [see Warnings and Precautions (5.2), Use in Specific Populations (8.1)]
- For use as post-coital contraception (emergency contraception)
- Congenital or acquired uterine anomaly, including fibroids, that distorts the uterine cavity
- Acute pelvic inflammatory disease (PID) or a history of PID unless there has been a subsequent intrauterine pregnancy [see Warnings and Precautions (5.4)]
- Postpartum endometritis or infected abortion in the past 3 months
- Known or suspected uterine or cervical malignancy
- Known or suspected breast cancer or other progestin-sensitive cancer, now or in the past
- Uterine bleeding of unknown etiology
- Untreated acute cervicitis or vaginitis, including bacterial vaginosis or other lower genital tract infections until infection is controlled
- Acute liver disease or liver tumor (benign or malignant)
- Conditions associated with increased susceptibility to pelvic infections [see Warnings and Precautions (5.4)]
- A previously inserted intrauterine device (IUD) that has not been removed
- Hypersensitivity to any component of this product [see Adverse Reactions (6.2) and Description (11.1)]

5 WARNINGS AND PRECAUTIONS

5.1 Risk of Ectopic Pregnancy

Evaluate women for ectopic pregnancy if they become pregnant with Kyleena in place because the likelihood of a pregnancy being ectopic is increased with Kyleena. Approximately one-half of pregnancies that occur with Kyleena in place are likely to be ectopic. Also consider the possibility of ectopic pregnancy in the case of lower abdominal pain, especially in association with missed menses or if an amenorrheic woman starts bleeding.

The incidence of ectopic pregnancy in clinical trials with Kyleena, which excluded women with a history of ectopic pregnancy, was approximately 0.2% per year. The risk of ectopic pregnancy in women who have a history of ectopic pregnancy and use Kyleena is unknown. Women with a previous history of ectopic pregnancy, tubal surgery or pelvic infection carry a higher risk of ectopic pregnancy. Ectopic pregnancy may result in loss of fertility.

5.2 Risks with Intrauterine Pregnancy

If pregnancy occurs while using Kyleena, remove Kyleena because leaving it in place may increase the risk of spontaneous abortion and preterm labor. Removal of Kyleena or probing of the uterus may also result in spontaneous abortion. In the event of an intrauterine pregnancy with Kyleena, consider the following:

Septic abortion

In patients becoming pregnant with an IUS in place, septic abortion—with septicemia, septic shock, and death—may occur.

Continuation of pregnancy

If a woman becomes pregnant with Kyleena in place and if Kyleena cannot be removed or the woman chooses not to have it removed, warn her that failure to remove Kyleena increases the risk of miscarriage, sepsis, premature labor and premature delivery. Advise her of isolated reports of virilization of the female fetus following local exposure to LNG during pregnancy with an LNG IUS in place [see Use in Specific Populations (8.1)]. Follow her pregnancy closely and advise her to report immediately any symptom that suggests complications of the pregnancy.

5.3 Sepsis

Severe infection or sepsis, including Group A streptococcal sepsis (GAS), have been reported following insertion of a LNG-releasing IUS. In some cases, severe pain occurred within hours of insertion followed by sepsis within days. Because death from GAS is more likely if treatment is delayed, it is important to be aware of these rare but serious infections. Aseptic technique during insertion of Kyleena is essential in order to minimize serious infections such as GAS.

5.4 Pelvic Infection

Promptly examine users with complaints of lower abdominal or pelvic pain, odorous discharge, unexplained bleeding, fever, genital lesions or sores. Remove Kyleena in cases of recurrent endometritis or pelvic inflammatory disease, or if an acute pelvic infection is severe or does not respond to treatment.

Pelvic Inflammatory Disease (PID)

Kyleena is contraindicated in the presence of known or suspected PID or in women with a history of PID unless there has been a subsequent intrauterine pregnancy [see Contraindications (4)]. IUDs have been associated with an increased risk of PID, most likely due to organisms being introduced into the uterus during insertion. In clinical trials, PID was observed in 0.5% of women overall and occurred more frequently within the first year and most often within the first month after insertion of Kyleena.

Women at increased risk for PID

PID is often associated with a sexually transmitted infection (STI), and Kyleena does not protect against STI. The risk of PID is greater for women who have multiple sexual partners, and also for women whose sexual partner(s) have multiple sexual partners. Women who have had PID are at increased risk for a recurrence or re-infection. In particular, ascertain whether the woman is at increased risk of infection (for example, leukemia, acquired immune deficiency syndrome [AIDS], intravenous drug abuse).

Subclinical PID

PID may be asymptomatic but still result in tubal damage and its sequelae.

Treatment of PID

Following a diagnosis of PID, or suspected PID, bacteriologic specimens should be obtained, and antibiotic therapy should be initiated promptly. Removal of Kyleena after initiation of antibiotic therapy is usually appropriate.^1

Actinomycosis

Actinomycosis has been associated with IUDs. Remove Kyleena from symptomatic women and treat with antibiotics. The significance of actinomyces-like organisms on Pap smear in an asymptomatic IUD user is unknown, and so this finding alone does not always require Kyleena removal and treatment. When possible, confirm a Pap smear diagnosis with cultures.

5.5 Perforation

Perforation (total or partial, including penetration/embedment of Kyleena in the uterine wall or cervix) may occur most often during insertion, although the perforation may not be detected until sometime later. The incidence of perforation during clinical trials was < 0.1%.

The risk of uterine perforation is increased in women who have recently given birth, and in women who are breastfeeding at the time of insertion. In a large postmarketing safety study conducted in the US, the risk of uterine perforation was highest when insertion occurred within ≤ 6 weeks postpartum, and also higher with breastfeeding at the time of insertion [see Adverse Reactions (6.2)].

The risk of perforation may be increased if Kyleena is inserted when the uterus is fixed, retroverted or not completely involuted.

If perforation occurs, locate and remove Kyleena. Surgery may be required. Delayed detection or removal of Kyleena in case of perforation may result in migration outside the uterine cavity, adhesions, peritonitis, intestinal perforations, intestinal obstruction, abscesses and erosion of adjacent viscera. In addition, perforation may reduce contraceptive efficacy and result in pregnancy.

5.6 Expulsion

Partial or complete expulsion of Kyleena may occur resulting in the loss of efficacy. Expulsion may be associated with symptoms of bleeding or pain, or it may be asymptomatic and go unnoticed. Kyleena typically decreases menstrual bleeding over time; therefore, an increase of menstrual bleeding may be indicative of an expulsion. Consider further diagnostic imaging, such as x-ray, if expulsion is suspected based on ultrasound [see Warnings and Precautions (5.10)]. In clinical trials, a 5-year expulsion rate of 3.5% (59 out of 1,690 subjects) was reported.

The risk of expulsion is increased with insertions immediately after delivery and appears to be increased with insertion after second-trimester abortion based on limited data. In a large postmarketing safety study conducted in the US, the risk of expulsion was lower with breastfeeding status [see Adverse Reactions (6.2)].

Remove a partially expelled Kyleena. If expulsion has occurred, a new Kyleena can be inserted any time the provider can be reasonably certain the woman is not pregnant.

5.7 Ovarian Cysts

Because the contraceptive effect of Kyleena is mainly due to its local effects within the uterus, ovulatory cycles with follicular rupture usually occur in women of fertile age using Kyleena. Ovarian cysts (reported as adverse reactions if they were abnormal, non-functional cysts and/or had a diameter >3 cm on ultrasound examination) were reported at least once over the course of clinical trials in 22% of women using Kyleena, and 0.6% of subjects discontinued because of an ovarian cyst. Most ovarian cysts are asymptomatic, although some may be accompanied by pelvic pain or dyspareunia. In most cases the ovarian cysts disappear spontaneously during two to three months observation. Evaluate persistent ovarian cysts. Surgical intervention is not usually required.

5.8 Bleeding Pattern Alterations

Kyleena can alter the bleeding pattern and result in spotting, irregular bleeding, heavy bleeding, oligomenorrhea and amenorrhea. During the first 3–6 months of Kyleena use, the number of bleeding and spotting days may be higher and bleeding patterns may be irregular. Thereafter, the number of bleeding and spotting days usually decreases but bleeding may remain irregular.

In Kyleena clinical trials, amenorrhea developed by the end of the first year of use in approximately 12% of Kyleena users. A total of 81 subjects out of 1,697 (4.8%) discontinued due to uterine bleeding complaints. Table 2 shows the bleeding patterns as documented in the Kyleena clinical trials based on 90-day reference periods. Table 3 shows the number of bleeding and spotting days based on 28-day cycle equivalents.

Table 2: Bleeding Patterns Reported with Kyleena in Contraception Studies (by 90-day reference periods)
Kyleena | First 90 days N=1,566 | Second 90 days N=1,511 | End of year 1 N=1,371 | End of year 3 N=975 | End of year 5; N=530
Amenorrhea^1 | <1% | 5% | 12% | 20% | 23%
Infrequent bleeding^2 | 10% | 20% | 26% | 26% | 26%
Frequent bleeding^3 | 25% | 10% | 4% | 2% | 2%
Prolonged bleeding^4 | 57% | 14% | 6% | 2% | 1%
Irregular bleeding^5 | 43% | 25% | 17% | 10% | 9%

^1Defined as subjects with no bleeding/spotting throughout the 90-day reference period

^2Defined as subjects with 1 or 2 bleeding/spotting episodes in the 90-day reference period

^3Defined as subjects with more than 5 bleeding/spotting episodes in the 90-day reference period

^4Defined as subjects with bleeding/spotting episodes lasting more than 14 days in the 90-day reference period. Subjects with prolonged bleeding may also be included in one of the other categories (excluding amenorrhea)

^5Defined as subjects with 3 to 5 bleeding/spotting episodes and less than 3 bleeding/spotting-free intervals of 14 or more days

Table 3: Mean number of Bleeding and Spotting Days per 28-day Cycle Equivalent
28-day Cycle Equivalent | Cycle 1; N=1,619 | Cycle 4; N=1,575 | Cycle 7; N=1,518 | Cycle 13; N=1,394 | Cycle 39; N=913 | Cycle 65; N=322
Days on treatment | 1–28 | 85–112 | 169–196 | 337–364 | 1065–1092 | 1793-1820
 | Mean (SD) | Mean (SD) | Mean (SD) | Mean (SD) | Mean (SD) | Mean (SD)
Number of bleeding days | 7.2 (5.9) | 3.2 (3.6) | 2.2 (3.0) | 1.5 (2.4) | 1.0 (2.0) | 0.9 (1.8)
Number of spotting days | 8.6 (6.0) | 4.6 (4.4) | 3.5 (3.4) | 2.9 (3.0) | 2.2 (2.6) | 2.1 (2.4)

If a significant change in bleeding develops during prolonged use, take appropriate diagnostic measures to rule out endometrial pathology. Consider the possibility of pregnancy if menstruation does not occur within six weeks of the onset of a previous menstruation. Once pregnancy has been excluded, repeated pregnancy tests are generally not necessary in amenorrheic women unless indicated, for example, by other signs of pregnancy or by pelvic pain.

5.9 Breast Cancer

Women who currently have or have had breast cancer, or have a suspicion of breast cancer, should not use hormonal contraception, including Kyleena, because some breast cancers are hormone-sensitive [see Contraindications (4)].

Spontaneous reports of breast cancer have been received during postmarketing experience with a LNG-releasing IUS. Observational studies of the risk of breast cancer with use of a LNG-releasing IUS do not provide conclusive evidence of increased risk.

5.10 Clinical Considerations for Use and Removal

Use Kyleena with caution after careful assessment if any of the following conditions exist, and consider removal of the system if any of them arise during use:

- Coagulopathy or use of anticoagulants
- Migraine, focal migraine with asymmetrical visual loss or other symptoms indicating transient cerebral ischemia
- Exceptionally severe headache
- Marked increase of blood pressure
- Severe arterial disease such as stroke or myocardial infarction

In addition, consider removing Kyleena if any of the following conditions arise during use:

- Uterine or cervical malignancy
- Jaundice

If the threads are not visible or are significantly shortened, they may have broken or retracted into the cervical canal or uterus. Consider the possibility that the system may have been displaced (for example, expelled or perforated the uterus) [see Warnings and Precautions (5.5, 5.6)]. Exclude pregnancy and verify the location of Kyleena, for example, by sonography, X-ray, or by gentle exploration of the cervical canal with a suitable instrument. If Kyleena is displaced, remove it. A new Kyleena may be inserted at that time or during the next menses if it is certain that conception has not occurred. If Kyleena is in place with no evidence of perforation, no intervention is indicated.

5.11 Magnetic Resonance Imaging (MRI) Safety Information

Non-clinical testing has demonstrated that Kyleena is MR Conditional. A patient with Kyleena can be safely scanned in an MR system meeting the following conditions:

- Static magnetic field of 3.0 T or less
- Maximum spatial field gradient of 36,000 gauss/cm (360 T/m)
- Maximum MR system reported, whole body averaged specific absorption rate (SAR) of 4W/kg (First Level Controlled Operating Mode)

Under the scan conditions defined above, the Kyleena IUS is expected to produce a maximum temperature rise of less than 2°C after 15 minutes of continuous scanning.

In non-clinical testing, the image artifact caused by the IUS extended up to 5 mm from the IUS when imaged with a gradient echo pulse sequence and a 3.0 T MRI system.

6 ADVERSE REACTIONS

The following serious or otherwise important adverse reactions are discussed elsewhere in the labeling:

- Ectopic Pregnancy [see Warnings and Precautions (5.1)]
- Intrauterine Pregnancy [see Warnings and Precautions (5.2)]
- Group A Streptococcal Sepsis (GAS) [see Warnings and Precautions (5.3)]
- Pelvic Inflammatory Disease [see Warnings and Precautions (5.4)]
- Perforation [see Warnings and Precautions (5.5)]
- Expulsion [see Warnings and Precautions (5.6]
- Ovarian Cysts [see Warnings and Precautions (5.7)]
- Bleeding Pattern Alterations [see Warnings and Precautions (5.8)]

6.1 Clinical Trials Experience

Because clinical trials are conducted under widely varying conditions, adverse reaction rates observed in the clinical trials of a drug cannot be directly compared to rates in the clinical trials of another drug and may not reflect the rates observed in clinical practice.

The data described below reflect exposure of 1,697 healthy 18 to 41-year-old women (mean age 27.8 ± 5.2 years) to Kyleena. These data come from two multi-center contraceptive trials: A phase 2 study with a 3-year duration was conducted in Europe enrolling generally healthy, 21 to 41-year old women; 217 subjects were exposed to Kyleena for one year and 174 completed three years. The data in this trial cover approximately 8,000 cycles of exposure. A phase 3 study with a 3-year duration and an optional extension of Kyleena use up to 5 years was conducted in the United States (US), Canada, Europe, and Latin America. The population was generally healthy, 18 to 35-year old women. A total of 1,208 subjects were exposed to Kyleena for at least one year; 707 women entered the optional extension phase after 3 years and 550 completed five years. The data in this trial cover approximately 60,000 cycles.

In total for both studies, 1,425 subjects were exposed for at least 1 year, and 550 subjects completed 5 years of use. Of the total of 1,697 subjects exposed to Kyleena, 563 were from the US and 1,134 were from Europe, Canada and Latin America; 623 (37%) were nulliparous (mean age 24.6 ± 4.5 years) and 1,074 (63%) were parous (mean age 29.7 ± 4.7 years). Most women who received Kyleena were Caucasian (83%) or Black/African American (4.4%); 9.4% of women were of Hispanic ethnicity. The clinical trials had no upper or lower weight or body mass index (BMI) limit. Mean BMI of Kyleena subjects was 25.2 kg/m2 (range 15.2 – 57.6 kg/m2); 16% had a BMI ≥ 30 kg/m2, and 2.0% had a BMI ≥ 40 kg/m2. The frequencies of reported adverse drug reactions represent crude incidences.

The most common adverse reactions (occurring in ≥ 5% users) were vulvovaginitis (24%), ovarian cyst (22%), abdominal pain/pelvic pain (21%), headache/migraine (15%), acne/seborrhea (15%), dysmenorrhea/uterine spasm (10%), breast pain/breast discomfort (10%), and increased bleeding (8%).

In the combined studies, 22% discontinued prematurely due to an adverse reaction. The most common adverse reactions (>1%) leading to discontinuation were increased bleeding (4.5%), abdominal pain/pelvic pain (4.2%), device expulsion (3.1%), acne/seborrhea (2.3%), and dysmenorrhea/uterine spasm (1.3%).

Common adverse reactions (occurring in ≥1% users) are summarized in Table 4 (presented as crude incidences).

Table 4: Adverse reactions that occurred in at least 1% of Kyleena users in clinical trials by System Organ Class (SOC)
System Organ Class | Adverse Reaction | Incidence (%) (N=1,697)
Reproductive System and Breast Disorders | Vulvovaginitis | 24.3
Reproductive System and Breast Disorders | Ovarian cysta | 22.2
Reproductive System and Breast Disorders | Dysmenorrhea/uterine spasm | 8.0/2.4
Reproductive System and Breast Disorders | Increased bleedingb | 7.9
Reproductive System and Breast Disorders | Breast pain/discomfort | 7.1/3.5
Reproductive System and Breast Disorders | Genital discharge | 4.5
Reproductive System and Breast Disorders | Device expulsion (complete and partial) | 3.5
Reproductive System and Breast Disorders | Upper genital tract infection | 1.5
Gastrointestinal Disorders | Abdominal pain/pelvic pain | 13.3/8.2
Gastrointestinal Disorders | Nausea | 4.7
Skin and Subcutaneous Tissue Disorders | Acne/Seborrhea | 14.1/1.8
Skin and Subcutaneous Tissue Disorders | Alopecia | 1.0
Nervous System Disorders | Headache/Migraine | 12.9/3.3
Psychiatric Disorders | Depression/ Depressed mood | 4.4/0.2

a Ovarian cysts were reported as adverse events if they were abnormal, non-functional cysts and/or had a diameter >3 cm on ultrasound examination

b Not all bleeding alterations were captured as adverse reactions [see Warnings and Precautions (5.8)].

In the clinical trials, serious adverse reactions occurring in more than a single subject included: ectopic pregnancy/ruptured ectopic pregnancy (10 subjects); pelvic inflammatory disease (6 subjects); missed abortion/incomplete spontaneous abortion/spontaneous abortion (4 subjects); ovarian cyst (3 subjects); abdominal pain (4 subjects); depression/affective disorder (4 subjects); and uterine perforation/embedded device (myometrial perforation) (3 subjects).

6.2 Postmarketing Experience

Adverse Reactions from Postmarketing Spontaneous Reports

The following adverse reactions have been identified during post-approval use of LNG-releasing IUSs. Because these reactions are reported voluntarily from a population of uncertain size, it is not always possible to reliably estimate their frequency or establish a causal relationship to drug exposure.

- Arterial thrombotic and venous thromboembolic events, including cases of pulmonary embolism, deep vein thrombosis and stroke
- Device breakage
- Hypersensitivity (including rash, urticaria, and angioedema)
- Increased blood pressure

Reported Adverse Reactions from Postmarketing Studies

Assessment of Perforation and Expulsion of Intrauterine Devices (APEX IUD) Study

APEX IUD was a large US retrospective cohort study to assess the impact of breastfeeding and timing of postpartum IUD insertion on uterine perforation and IUD expulsion. The analyses included a total of 326,658 insertions, 30% (97,824 insertions) of which were performed in women with a delivery in the previous 12 months. For insertions performed in women who had delivered ≤ 52 weeks before IUD insertion, the majority of postpartum insertions, 57.3% (56,047 insertions) occurred between 6 and 14 weeks postpartum. Breastfeeding data were available in 94,817 insertions performed in women 52 weeks or less after delivery.

The study results indicated that the risk of uterine perforation was highest in women with IUD insertion ≤ 6 weeks postpartum. Immediate postpartum insertion (0–3 days) findings are limited due to the relatively small number of insertions occurring within this time interval. Women who were breastfeeding at the time of insertion were at 33% higher risk of perforation (adjusted hazard ratio [HR]=1.33, 95% confidence interval [CI]: 1.07–1.64) compared to women who were not breastfeeding at the time of insertion. Progressively lower risk of uterine perforation was observed in postpartum time windows beyond 6 weeks, in both breastfeeding and not breastfeeding women. Table 5 presents the uterine perforation rates for LNG IUS stratified by breastfeeding status and postpartum interval.

Table 5: Uterine Perforation^1 rates for LNG IUS, by Breastfeeding Status and Postpartum Interval
 | Breastfeeding at time of insertion |  | Not breastfeeding at time of insertion
Postpartum interval at time of insertion | Number of events/ insertions | Uterine perforation rate per 1,000 insertions | Number of events/ insertions | Uterine perforation rate per 1,000 insertions
0 to 3 days | 8/1,896 | 4.22 | 0/277 | 0.00
4 days to ≤ 6 weeks | 120/10,735 | 11.18 | 28/2,377 | 11.78
> 6 to ≤ 14 weeks | 268/29,677 | 9.03 | 80/12,011 | 6.66
> 14 to ≤ 52 weeks | 43/6,139 | 7.00 | 22/9,089 | 2.42
> 52 weeks or no delivery | no data available |  | 243/184,733 | 1.32

^1Uterine perforation includes both complete and partial perforation

Risk of expulsion was variable over the postpartum intervals through 52 weeks. Women who were breastfeeding were at 28% lower risk of IUD expulsion (adjusted HR=0.72, 95% CI: 0.64-0.80) compared to women who were not breastfeeding at time of insertion. Table 6 presents the IUD expulsion rates for LNG IUS stratified by breastfeeding status and postpartum interval.

Table 6: Expulsion^1 Rates for LNG IUS, by Breastfeeding Status and Postpartum Interval
 | Breastfeeding at time of insertion |  | Not breastfeeding at time of insertion
Postpartum interval at time of insertion | Number of events/ insertions | Expulsion rate per 1,000 insertions | Number of events/ insertions | Expulsion rate per 1,000 insertions
0 to 3 days | 187/1,896 | 98.63 | 12/277 | 43.32
4 days to ≤ 6 weeks | 185/10,735 | 17.23 | 52/2,377 | 21.88
> 6 to ≤ 14 weeks | 421/29,677 | 14.19 | 306/12,011 | 25.48
> 14 to ≤ 52 weeks | 120/6,139 | 19.55 | 273/9,089 | 30.04
> 52 weeks or no delivery | no data available |  | 5,481/184,733 | 29.67

^1Expulsion includes both complete and partial expulsion

7 DRUG INTERACTIONS

No drug-drug interaction studies have been conducted with Kyleena.

Drugs or herbal products that induce or inhibit LNG metabolizing enzymes, including CYP3A4, may decrease or increase, respectively, the serum concentrations of LNG during the use of Kyleena. However, the contraceptive effect of Kyleena is mediated via the direct release of LNG into the uterine cavity and is unlikely to be affected by drug interactions via enzyme induction or inhibition.

8 USE IN SPECIFIC POPULATIONS

8.1 Pregnancy

Risk Summary

The use of Kyleena is contraindicated in pregnancy or with a suspected pregnancy and Kyleena may cause adverse pregnancy outcomes [see Contraindications (4), Warnings and Precautions (5.1, 5.2)]. If a woman becomes pregnant with Kyleena in place, the likelihood of ectopic pregnancy is increased and there is an increased risk of miscarriage, sepsis, premature labor, and premature delivery. Remove Kyleena, if possible, if pregnancy occurs in a woman using Kyleena. If Kyleena cannot be removed, follow the pregnancy closely [see Warnings and Precautions (5.1, 5.2)].

There have been isolated cases of virilization of the external genitalia of the female fetus following local exposure to LNG during pregnancy with an LNG IUS in place. Animal reproduction studies have not been conducted with Kyleena.

8.2 Lactation

Risk Summary

Published studies report the presence of LNG in human milk. Small amounts of progestins (approximately 0.1% of the total maternal doses) were detected in the breast milk of nursing mothers who used other LNG-releasing IUSs, resulting in exposure of LNG to the breastfed infants. There are no reports of adverse effects in breastfed infants with maternal use of progestin-only contraceptives. Isolated cases of decreased milk production have been reported with a LNG-releasing IUS. The developmental and health benefits of breastfeeding should be considered along with the mother's clinical need for Kyleena and any potential adverse effects on the breastfed child from Kyleena or from the underlying maternal condition.

8.3 Females and Males of Reproductive Potential

Return to Fertility After Discontinuing Kyleena

About 71% of 163 women who desired pregnancy after study discontinuation and provided follow-up information, conceived within 12 months after removal of Kyleena.

8.4 Pediatric Use

Safety and efficacy of Kyleena have been established in women of reproductive age. Efficacy is expected to be the same for postpubertal females under the age of 18 as for users 18 years and older. Use of this product before menarche is not indicated.

8.5 Geriatric Use

Kyleena has not been studied in women over age 65 and is not approved for use in this population.

11 DESCRIPTION

Kyleena (levonorgestrel-releasing intrauterine system) contains 19.5 mg of LNG, a progestin, and is intended to provide an initial release rate of approximately17.5 mcg/day of LNG after 24 days.

Levonorgestrel USP, (-)-13-Ethyl-17-hydroxy-18,19-dinor-17α-pregn-4-en-20-yn-3-one, the active ingredient in Kyleena, has a molecular weight of 312.4, a molecular formula of C21H28O2, and the following structural formula:

11.1 Kyleena

Kyleena consists of a T-shaped polyethylene frame (T-body) with a steroid reservoir (hormone elastomer core) around the vertical stem. The white T-body has a loop at one end of the vertical stem and two horizontal arms at the other end. The reservoir consists of a whitish or pale yellow cylinder, made of a mixture of LNG and silicone (polydimethylsiloxane), containing a total of 19.5 mg LNG. The reservoir is covered by a semi-opaque silicone membrane, composed of polydimethylsiloxane and colloidal silica. A ring composed of 99.95% pure silver is located at the top of the vertical stem close to the horizontal arms and is visible by ultrasound. The polyethylene of the T-body is compounded with barium sulfate, which makes it radiopaque. A monofilament blue polypropylene removal thread is attached to a loop at the end of the vertical stem of the T-body. The polypropylene of the removal thread contains <0.5% phthalocyaninato(2-) copper as a colorant (see Figure 10).

The components of Kyleena, including its packaging, are not manufactured using natural rubber latex.

Figure 10. Kyleena

11.2 Inserter

Kyleena is packaged sterile within an inserter. The inserter (Figure 11), which is used for insertion of Kyleena into the uterine cavity, consists of a symmetric two-sided body and slider that are integrated with flange, lock, pre-bent insertion tube and plunger. The outer diameter of the insertion tube is 3.8 mm. The vertical stem of Kyleena is loaded in the insertion tube at the tip of the inserter. The arms are pre-aligned in the horizontal position. The removal threads are contained within the insertion tube and handle. Once Kyleena has been placed, the inserter is discarded.

Figure 11. Diagram of Inserter

12 CLINICAL PHARMACOLOGY

12.1 Mechanism of Action

The local mechanism by which continuously released LNG contributes to the contraceptive effectiveness of Kyleena has not been conclusively demonstrated. Studies of Kyleena and similar LNG IUS prototypes have suggested several mechanisms that prevent pregnancy: thickening of cervical mucus preventing passage of sperm into the uterus, inhibition of sperm capacitation or survival, and alteration of the endometrium.

12.2 Pharmacodynamics

Kyleena has mainly local progestogenic effects in the uterine cavity. The local concentrations of LNG lead to morphological changes including stromal pseudodecidualization, glandular atrophy, a leukocytic infiltration and a decrease in glandular and stromal mitoses.

In clinical trials with Kyleena, ovulation was assessed based on serum progesterone values >2.5 ng/mL in one study and serum progesterone values >2.5 ng/mL together with serum estradiol levels <27.24 pg/mL in another study. Evidence of ovulation by these criteria was seen in 23 out of 26 women in the first year, in 19 out of 20 women in the second year, and in all 16 women in the third year. In the fourth year, evidence of ovulation was observed in the one woman remaining in the subset and in the fifth year, no women remained in this subset.

12.3 Pharmacokinetics

Absorption

Low doses of LNG are administered into the uterine cavity with the Kyleena intrauterine delivery system. The in vivo release rate is approximately 17.5 mcg/day after 24 days and is reduced to approximately 15.3 mcg/day after 60 days and to 9.8 mcg/day after 1 year. It then declines progressively to approximately 7.9 mcg/day after 3 years and 7.4 mcg/day after 5 years. The average LNG in vivo release rate is approximately 12.6 mcg/day over the first year and 9.0 mcg/day over the period of 5 years.

In a subset of 6 subjects, the maximum observed serum LNG concentration (mean ±SD) was 302 ± 170 pg/mL, reached after 7.5 days (median) of Kyleena insertion. Thereafter, the LNG serum concentrations (mean ±SD) at Year 1, 2, 3, 4 and 5 were 199 ± 171 pg/mL (N=6), 120 ± 57 pg/mL (N=6), 122 ± 65 pg/mL (N=6), 79 ± 12 pg/mL (N=3) and 65 ± 15 pg/mL (N=3), respectively. A population pharmacokinetic evaluation based on a broader database (>1000 patients) showed a similar declining concentration profile, with 175 ± 74 pg/mL at 7 days after placement, 125 ± 50 pg/mL at 1 year, 99 ± 41 pg/mL after 3 years, and 90 ± 35 pg/mL after 5 years.

Distribution

The apparent volume of distribution of LNG is reported to be approximately 1.8 L/kg. LNG is bound non-specifically to serum albumin and specifically to sex hormone binding globulin (SHBG). Accordingly, changes in the concentration of SHBG in serum result in an increase (at higher SHBG concentration) or a decrease (at lower SHBG concentration) of the total LNG concentration in serum. In a subset of 6 subjects, the concentration of SHBG declined on average by about 30% during the first 3 months after insertion of Kyleena and remained relatively stable over the 5 year period of use. Less than 2% of the circulating LNG is present as free steroid.

Elimination

Following intravenous administration of 0.09 mg LNG to healthy volunteers, the total clearance of LNG is approximately 1 mL/min/kg and the elimination half-life is approximately 20 hours. Metabolic clearance rates may differ among individuals by several-fold, and this may account in part for wide individual variations in LNG concentrations seen in individuals using LNG–containing contraceptive products.

Metabolism

Following absorption, LNG is extensively metabolized. The most important metabolic pathways are the reduction of the Δ4-3-oxo group and hydroxylations at positions 2α, 1β and 16β, followed by conjugation. Significant amounts of conjugated and unconjugated 3α, 5β- are also present in serum, along with much smaller amounts of 3α, 5α-tetrahydrolevonorgestrel and 16β-hydroxylevonorgestrel. CYP3A4 is the main enzyme involved in the oxidative metabolism of LNG.

Excretion

LNG and its phase I metabolites are excreted primarily as glucuronide conjugates. About 45% of LNG and its metabolites are excreted in the urine and about 32% are excreted in feces, mostly as glucuronide conjugates.

Specific Populations

Pediatric: Safety and efficacy of Kyleena have been established in women of reproductive age. Use of this product before menarche is not indicated.

Geriatric: Kyleena has not been studied in women over age 65 and is not approved for use in this population.

Race: No studies have evaluated the effect of race on the pharmacokinetics of Kyleena.

Hepatic Impairment: No studies were conducted to evaluate the effect of hepatic disease on the disposition of Kyleena.

Renal Impairment: No formal studies were conducted to evaluate the effect of renal disease on the disposition of Kyleena.

Drug-Drug Interactions

No drug-drug interaction studies were conducted with Kyleena [see Drug Interactions (7)].

13 NONCLINICAL TOXICOLOGY

13.1 Carcinogenesis, Mutagenesis, Impairment of Fertility

[See Warnings and Precautions (5.9).]

14 CLINICAL STUDIES

The contraceptive efficacy of Kyleena was evaluated in a clinical trial that enrolled generally healthy women aged 18–35, of whom 1,452 received Kyleena. Of these, 40% (574) were nulliparous women, 870 (60%) women completed 3 years of the study, 707 (49%) elected to enroll in an extension phase up to a total of 5 years, and 550 (38%) completed 5 years of use. The trial was a multicenter, multi-national, randomized, open-label study conducted in 11 countries in Europe, Latin America, the US and Canada. Women less than six weeks postpartum, with a history of ectopic pregnancy, with clinically significant ovarian cysts or with HIV or otherwise at high risk for sexually transmitted infections were excluded. A total of 563 (39%) were treated at US sites and 889 (61%) were at non-US sites. The racial demographics of enrolled women who received Kyleena was: Caucasian (80%), Black/African American (5.1%), Other (2.6%) and Asian (1.2%); 11% indicated Hispanic ethnicity. The clinical trial had no upper or lower weight or BMI limit. The weight range was 38 to 173 kg (mean weight: 68.7 kg) and mean BMI was 25.3 kg/m^2 (range 15.2–57.6 kg/m^2). Of Kyleena-treated women, 22% discontinued the study treatment due to an adverse reaction, 5.0% were lost to follow-up, 2.3% withdrew for unspecified reasons, 1.2% discontinued due to a protocol deviation, 0.9% discontinued due to pregnancy, and 20% discontinued due to other reasons.

The pregnancy rate calculated as the Pearl Index (PI) in women aged 18–35 years was the primary efficacy endpoint used to assess contraceptive reliability. The PI was calculated based on 28-day equivalent exposure cycles; evaluable cycles excluded those in which back-up contraception was used unless a pregnancy occurred in that cycle. The Year 1 PI was based on 2 pregnancies and the cumulative 5-year pregnancy rate was based on 13 pregnancies that occurred after the onset of treatment and within 7 days after Kyleena removal or expulsion. Table 5 shows the calculated annual and cumulative pregnancy rates.

Table 7: Pearl Indices by Year and 5-Year Cumulative Pregnancy Rate
Kyleena Clinical Trial | Pearl Index |  |  |  |  | Cumulative 5-Year Kaplan Meier Rate
Kyleena Clinical Trial | Year 1 | Year 2 | Year 3 | Year 4 | Year 5 | Cumulative 5-Year Kaplan Meier Rate
Number of Evaluable 28-day Cycles of Exposure | 16,207 | 13,853 | 11,610 | 8,556 | 7,087 | 57,313
Pregnancy Rate (95% Confidence Interval) | 0.16; (0.02, 0.58) | 0.38; (0.10, 0.96) | 0.45; (0.12, 1.15) | 0.15; (0.00, 0.85) | 0.37; (0.04, 1.33) | 1.45; (0.82, 2.53)

15 REFERENCES

^1Centers for Disease Control and Prevention (CDC), (2019). CDC-STD Treatment [online] Available at: https://www.cdc.gov/std/treatment/default.htm

16 HOW SUPPLIED/STORAGE AND HANDLING

Kyleena (levonorgestrel-releasing intrauterine system), containing a total of 19.5 mg LNG, is available in a carton of one sterile unit. NDC# 50419-424-01

Kyleena is supplied sterile. Kyleena is sterilized with ethylene oxide. Do not resterilize. For single use only. Do not use if the inner package is damaged or open. Insert before the end of the month shown on the label.

Store at 25°C (77°F); with excursions permitted between 15–30°C (59–86°F) [see USP Controlled Room Temperature].

17 PATIENT COUNSELING INFORMATION

Advise the patient to read the FDA-approved patient labeling (Patient Information).

- Sexually Transmitted Infections: Advise the patient that this product does not protect against HIV infection (AIDS) and other sexually transmitted infections (STIs).
- Risk of Ectopic Pregnancy: Advise the patient about the risks of ectopic pregnancy, including the loss of fertility. Teach her to recognize and report to her healthcare provider promptly any symptoms of ectopic pregnancy. [See Warnings and Precautions (5.1).]
- Risks of Intrauterine Pregnancy: Advise the patient to contact her healthcare provider if she thinks she might be pregnant. Inform the patient about the risks of intrauterine pregnancy while using Kyleena, including the risks of leaving Kyleena in place and the risks of removing Kyleena or probing of the uterus. If Kyleena cannot be removed in a pregnant patient, advise her to report immediately any symptom that suggests complications of the pregnancy. Advise her of isolated reports of virilization of the female fetus following local exposure to LNG during pregnancy with an LNG IUS in place. [See Warnings and Precautions (5.2) and Use in Special Populations (8.1).]
- Sepsis: Advise the patient that severe infection or sepsis, including Group A streptococcal sepsis (GAS), can occur within the first few days after Kyleena is inserted. Instruct her to contact a healthcare provider immediately if she develops severe pain or fever shortly after Kyleena is inserted. [See Warnings and Precautions (5.3).]
- Pelvic Infection: Advise the patient about the possibility of pelvic infections, including PID, and that these infections can cause tubal damage leading to ectopic pregnancy or infertility, or infrequently can necessitate hysterectomy, or cause death. Teach patients to recognize and report to their healthcare provider promptly any symptoms of pelvic infection. These symptoms include development of menstrual disorders (prolonged or heavy bleeding), unusual vaginal discharge, abdominal or pelvic pain or tenderness, dyspareunia, chills, and fever. [See Warnings and Precautions (5.4).]
- Perforation and Expulsion: Advise the patient that the IUS may be expelled from or perforate the uterus and instruct her on how she can check that the threads still protrude from the cervix. Inform her that excessive pain or vaginal bleeding during Kyleena placement, worsening pain or bleeding after placement, or the inability to feel Kyleena strings may occur with Kyleena perforation and expulsion. Caution her not to pull on the threads and displace Kyleena. Inform her that there is no contraceptive protection if Kyleena is displaced or expelled. Instruct the patient to contact her healthcare provider if she cannot feel the threads and to avoid intercourse or use a non-hormonal back-up birth control (such as condoms or spermicide) until the location of Kyleena has been confirmed. Advise her that if perforation occurs, Kyleena will have to be located and removed; surgery may be required. [See Warnings and Precautions (5.5, 5.6, 5.10).]
- Ovarian Cysts: Advise the patient regarding the risk of ovarian cysts and that cysts can cause clinical symptoms including pelvic pain, abdominal pain or dyspareunia. Advise the patient to contact her healthcare provider if she experiences these symptoms. [See Warnings and Precautions (5.7).]
- Bleeding Pattern Alterations: Advise the patient that irregular or prolonged bleeding and spotting, and/or cramps may occur during the first few weeks after insertion. Inform the patient that, during the first 6 months of Kyleena use, the number of bleeding and spotting days may be higher and bleeding patterns may be irregular. If her symptoms continue or are severe she should report them to her healthcare provider. [See Warnings and Precautions (5.8).]
- Clinical Considerations for Use and Removal: Advise the patient to contact her healthcare provider if she experiences any of the following:
- A stroke or heart attack
- Very severe or migraine headaches
- Unexplained fever
- Yellowing of the skin or whites of the eyes, as these may be signs of serious liver problems
- Pregnancy or suspected pregnancy
- Pelvic pain, abdominal pain, or pain during sex
- HIV positive seroconversion in herself or her partner
- Possible exposure to STIs
- Unusual vaginal discharge or genital sores
- Severe vaginal bleeding or bleeding that lasts a long time, or if she misses a menstrual period
- Inability to feel Kyleena's threads
- Magnetic Resonance Imaging (MRI) Safety Information: Inform the patient that Kyleena can be safely scanned with MRI only under specific conditions [see Warnings and Precautions (5.11)]. Instruct patients who will have an MRI to tell their doctor that they have Kyleena.
Manufactured for:
Bayer HealthCare Pharmaceuticals Inc.
  Whippany, NJ 07981
© 2016, Bayer HealthCare Pharmaceuticals Inc.
  All rights reserved.

Patient Package Insert

Patient Information

Kyleena (Ki-lee-nah)

(levonorgestrel-releasing intrauterine system)

Read this Patient Information carefully before you decide if Kyleena is right for you. This information does not take the place of talking with your gynecologist or other healthcare provider who specializes in women's health. If you have any questions about Kyleena, ask your healthcare provider. You should also learn about other birth control methods to choose the one that is best for you.

Kyleena does not protect against HIV infection (AIDS) and other sexually transmitted infections (STIs).

What is Kyleena?

- Kyleena is a hormone-releasing system placed in your uterus by your healthcare provider to prevent pregnancy for up to 5 years.
- Kyleena can be removed by your healthcare provider at any time.
- Kyleena can be used whether or not you have given birth to a child.

Kyleena is a small, flexible plastic T-shaped system that slowly releases a progestin hormone called levonorgestrel (LNG) that is often used in birth control pills. Because Kyleena releases LNG into your uterus, only small amounts of the hormone enter your blood. Kyleena does not contain estrogen.

Two thin threads are attached to the stem (lower end) of Kyleena. The threads are the only part of Kyleena you can feel when Kyleena is in your uterus; however, unlike a tampon string, the threads do not extend outside your body.

Kyleena is small

and Flexible

What if I need birth control for more than 5 years?

Kyleena must be removed after 5 years. Your healthcare provider can place a new Kyleena during the same office visit if you choose to continue using Kyleena.

What if I want to stop using Kyleena?

Kyleena is intended for use up to 5 years, but you can stop using Kyleena at any time by asking your healthcare provider to remove it. You could become pregnant as soon as Kyleena is removed, so you should use another method of birth control if you do not want to become pregnant. Talk to your healthcare provider about the best birth control methods for you, because your new method may need to be started 7 days before Kyleena is removed to prevent pregnancy.

What if I change my mind about birth control and want to become pregnant in less than 5 years?

Your healthcare provider can remove Kyleena at any time. You may become pregnant as soon as Kyleena is removed. About 7 out of 10 women who want to become pregnant will become pregnant sometime in the first year after Kyleena is removed.

How does Kyleena work?

Kyleena may work in several ways including thickening cervical mucus, inhibiting sperm movement, reducing sperm survival, and thinning the lining of your uterus. It is not known exactly how these actions work together to prevent pregnancy.

How well does Kyleena work for contraception?

The following chart shows the chance of getting pregnant for women who use different methods of birth control. Each box on the chart contains a list of birth control methods that are similar in effectiveness. The most effective methods are at the top of the chart. The box on the bottom of the chart shows the chance of getting pregnant for women who do not use birth control and are trying to get pregnant.

Kyleena, an intrauterine device (IUD), also known as an intrauterine system (IUS), is in the box at the top of the chart.

Who might use Kyleena?

You might choose Kyleena if you:

- want long-term birth control that provides a low chance of getting pregnant (less than 1 in 100)
- want birth control that works continuously for up to 5 years
- want birth control that is reversible
- want a birth control method that you do not need to take daily
- are willing to use a birth control method that is placed in the uterus
- want birth control that does not contain estrogen

Do not use Kyleena if you:

- are or might be pregnant; Kyleena cannot be used as an emergency contraceptive
- have a serious pelvic infection called pelvic inflammatory disease (PID) or have had PID in the past unless you have had a normal pregnancy after the infection went away
- have an untreated genital infection now
- have had a serious pelvic infection in the past 3 months after a pregnancy
- can get infections easily. For example, if you:
- have multiple sexual partners or your partner has multiple sexual partners
- have problems with your immune system
- use or abuse intravenous drugs
- have or suspect you might have cancer of the uterus or cervix
- have bleeding from the vagina that has not been explained
- have liver disease or a liver tumor
- have breast cancer or any other cancer that is sensitive to progestin (a female hormone), now or in the past
- have an intrauterine device in your uterus already
- have a condition of the uterus that changes the shape of the uterine cavity, such as large fibroid tumors
- are allergic to levonorgestrel, silicone, polyethylene, silver, silica, barium sulfate, polypropylene, or copper phthalocyanine

Before having Kyleena placed, tell your healthcare provider about all of your medical conditions including if you:

- have any of the conditions listed above
- have had a heart attack
- have had a stroke
- were born with heart disease or have problems with your heart valves
- have problems with blood clotting or take medicine to reduce clotting
- have high blood pressure
- recently had a baby or are breastfeeding
- have severe headaches or migraine headaches
- have AIDS, HIV, or any other sexually transmitted infection

Tell your healthcare provider about all of the medicines you take, including prescription and over-the-counter medicines, vitamins, and herbal supplements.

How is Kyleena placed?

Kyleena is placed by your healthcare provider during an in-office visit or immediately after giving birth.

First, your healthcare provider will examine your pelvis to find the exact position of your uterus. Your healthcare provider will then clean your vagina and cervix with an antiseptic solution and slide a slim plastic tube containing Kyleena through the cervix into your uterus. Your healthcare provider will then remove the plastic tube, and leave Kyleena in your uterus. Your healthcare provider will cut the threads to the right length.

You may experience pain, bleeding or dizziness during and after placement. If your symptoms do not pass within 30 minutes after placement, Kyleena may not have been placed correctly. Your healthcare provider will examine you to see if Kyleena needs to be removed or replaced.

Should I check that Kyleena is in place?

Yes, you should check that Kyleena is in proper position by feeling the removal threads. It is a good habit to do this 1 time a month. Your healthcare provider should teach you how to check that Kyleena is in place. First, wash your hands with soap and water. You can check by reaching up to the top of your vagina with clean fingers to feel the removal threads. Do not pull on the threads. If you feel more than just the threads or if you cannot feel the threads, Kyleena may not be in the right position and may not prevent pregnancy. Avoid intercourse or use non-hormonal back-up birth control (such as condoms or spermicide) and ask your healthcare provider to check that Kyleena is still in the right place.

How soon after placement of Kyleena should I return to my healthcare provider?

Call your healthcare provider if you have any questions or concerns (see "When should I call my healthcare provider?"). Otherwise, you should return to your healthcare provider for a follow-up visit 4 to 6 weeks after Kyleena is placed to make sure that Kyleena is in the right position.

Can I use tampons or menstrual cups with Kyleena?

Yes, tampons or menstrual cups may be used with Kyleena. Change tampons or menstrual cups with care to avoid pulling the threads of Kyleena. If you think you may have pulled Kyleena out of place, avoid intercourse or use a non-hormonal back-up birth control (such as condoms or spermicide), and contact your healthcare provider.

What if I become pregnant while using Kyleena?

Call your healthcare provider right away if you think you may be pregnant. If possible, also do a urine pregnancy test. If you get pregnant while using Kyleena, you may have an ectopic pregnancy. This means that the pregnancy is not in the uterus. Unusual vaginal bleeding or abdominal pain may be a sign of ectopic pregnancy.

Ectopic pregnancy is a medical emergency that often requires surgery. Ectopic pregnancy can cause internal bleeding, infertility, and even death.

There are also risks if you get pregnant while using Kyleena and the pregnancy is in the uterus. Severe infection, miscarriage, premature delivery, and even death can occur with pregnancies that continue with an intrauterine device (IUD). Because of this, your healthcare provider may try to remove Kyleena, even though removing it may cause a miscarriage. If Kyleena cannot be removed, talk with your healthcare provider about the benefits and risks of continuing the pregnancy and possible effects of the hormone on your unborn baby.

If you continue your pregnancy, see your healthcare provider regularly. Call your healthcare provider right away if you get flu-like symptoms, fever, chills, cramping, pain, bleeding, vaginal discharge, or fluid leaking from your vagina. These may be signs of infection.

How will Kyleena change my periods?

For the first 3 to 6 months, your period may become irregular and the number of bleeding days may increase. You may also have frequent spotting or light bleeding. Some women have heavy bleeding during this time. You may also have cramping during the first few weeks. After you have used Kyleena for a while, the number of bleeding and spotting days is likely to lessen. For some women, periods will stop altogether. When Kyleena is removed, your menstrual periods should return.

Is it safe to breastfeed while using Kyleena?

You may use Kyleena when you are breastfeeding. Kyleena is not likely to affect the quality or amount of your breast milk or the health of your nursing baby. However, isolated cases of decreased milk production have been reported. The risk of Kyleena going into the wall of the uterus (becoming embedded) or going through the wall of the uterus is increased if Kyleena is inserted while you are breastfeeding.

Will Kyleena interfere with sexual intercourse?

You and your partner should not feel Kyleena during intercourse. Kyleena is placed in the uterus, not in the vagina. Sometimes your partner may feel the threads. If this occurs, or if you or your partner experience pain during sex, talk with your healthcare provider.

Can I have an MRI with Kyleena in place?

Kyleena can be safely scanned with MRI only under specific conditions. Before you have an MRI, tell your healthcare provider that you have Kyleena, an intrauterine device (IUD), in place.

What are the possible side effects of Kyleena?

Kyleena can cause serious side effects including:

- Ectopic pregnancy and intrauterine pregnancy risks. There are risks if you become pregnant while using Kyleena (see "What if I become pregnant while using Kyleena?").
- Life-threatening infection. Life-threatening infection can occur within the first few days after Kyleena is placed. Call your healthcare provider immediately if you develop severe pain or fever shortly after Kyleena is placed.
- Pelvic inflammatory disease (PID). Some IUD users get a serious pelvic infection called pelvic inflammatory disease. PID is usually sexually transmitted. You have a higher chance of getting PID if you or your partner has sex with other partners. PID can cause serious problems such as infertility, ectopic pregnancy or pelvic pain that does not go away. PID is usually treated with antibiotics. More serious cases of PID may require surgery including removal of the uterus (hysterectomy). In rare cases, infections that start as PID can even cause death.
Tell your healthcare provider right away if you have any of these signs of PID: long-lasting or heavy bleeding, unusual vaginal discharge, low abdominal (stomach area) pain, painful sex, chills, fever, genital lesions or sores.
- Perforation. Kyleena may go into the wall of the uterus (become embedded) or go through the wall of the uterus. This is called perforation. If this occurs, Kyleena may no longer prevent pregnancy. If perforation occurs, Kyleena may move outside the uterus and can cause internal scarring, infection, or damage to other organs, and you may need surgery to have Kyleena removed. Excessive pain or vaginal bleeding during placement of Kyleena, pain or bleeding that gets worse after placement, or not being able to feel the threads may happen with perforation. The risk of perforation is increased if Kyleena is inserted while you are breastfeeding, or if you have recently given birth.
- Expulsion. Kyleena may come out by itself. This is called expulsion. Expulsion occurs in about 4 out of 100 women. Excessive pain or vaginal bleeding during placement of Kyleena, pain or bleeding that gets worse after placement, or not being able to feel the threads may happen with expulsion. You may become pregnant if Kyleena comes out. If you think that Kyleena has come out, avoid intercourse or use a non-hormonal back-up birth control (such as condoms or spermicide) and call your healthcare provider. The risk of expulsion is increased with insertion right after delivery or second-trimester abortion.

Common side effects of Kyleena include:

- Pain, bleeding or dizziness during and after placement. If these symptoms do not stop 30 minutes after placement, Kyleena may not have been placed correctly. Your healthcare provider will examine you to see if Kyleena needs to be removed or replaced.
- Changes in bleeding. You may have bleeding and spotting between menstrual periods, especially during the first 3–6 months. Sometimes the bleeding is heavier than usual at first. However, the bleeding usually becomes lighter than usual and may be irregular. Call your healthcare provider if the bleeding remains heavier than usual or increases after it has been light for a while.
- Missed menstrual periods. About 12 out of 100 women stop having periods after 1 year of Kyleena use. If you have any concerns that you may be pregnant while using Kyleena, do a urine pregnancy test and call your healthcare provider. If you do not have a period for 6 weeks during Kyleena use, call your healthcare provider. When Kyleena is removed, your menstrual periods should return.
- Cysts on the ovary. About 22 out of 100 women using Kyleena develop a cyst on the ovary. These cysts usually disappear on their own in 2 to 3 months. However, cysts can cause pain and sometimes cysts will need surgery.

Other common side effects include:

- inflammation or infection of the outer part of your vagina (vulvovaginitis)
- abdominal or pelvic pain
- headache or migraine
- acne or greasy skin
- painful periods
- sore or painful breasts

These are not all of the possible side effects with Kyleena. For more information, ask your healthcare provider.

Call your doctor for medical advice about side effects. You may report side effects to FDA at 1-800-FDA-1088. You may also report side effects to Bayer Healthcare Pharmaceuticals at 1-888-842-2937.

After Kyleena has been placed, when should I call my healthcare provider?

If Kyleena is accidentally removed and you had vaginal intercourse within the preceding week, you may be at risk of pregnancy, and you should talk to a healthcare provider.

Call your healthcare provider if you have any concerns about Kyleena. Be sure to call if you:

- think you are pregnant
- have pelvic pain, abdominal pain, or pain during sex
- have unusual vaginal discharge or genital sores
- have unexplained fever, flu-like symptoms or chills
- might be exposed to sexually transmitted infections (STIs)
- are concerned that Kyleena may have been expelled (came out)
- cannot feel Kyleena's threads
- develop very severe or migraine headaches
- have yellowing of the skin or whites of the eyes. These may be signs of liver problems.
- have had a stroke or heart attack
- become HIV positive or your partner becomes HIV positive
- have severe vaginal bleeding or bleeding that lasts a long time or concerns you

General advice about the safe and effective use of Kyleena.

Medicines are sometimes prescribed for conditions other than those listed in patient information leaflets. If you would like more information, talk with your healthcare provider. You can ask your healthcare provider for information about Kyleena that is written for health professionals.

What are the ingredients in KYLEENA?

Active ingredient: levonorgestrel

Inactive ingredients: silicone, polyethylene, silver, silica, barium sulfate, polypropylene, copper phthalocyanine

Manufactured for:

Bayer HealthCare Pharmaceuticals Inc.
Whippany, NJ 07981

© 2016, Bayer HealthCare Pharmaceuticals Inc.
All rights reserved.

For more information, go to www.Kyleena.com or call 1-888-842-2937

This Patient Information has been approved by the U.S. Food and Drug Administration.7/2021

PACKAGE/LABEL PRINCIPAL DISPLAY PANEL

NDC 50419-424-011
Sterile Unit
Rx only

www.kyleena.com

IMPORTANT: To be inserted in the uterus by or under the supervision of a licensed clinician. See physician insert for detailed instructions for use.

Kyleena

(levonorgestrel-releasing intrauterine system)

— 19.5 mg levonorgestrel

— 1 sterile unit

— intrauterine use